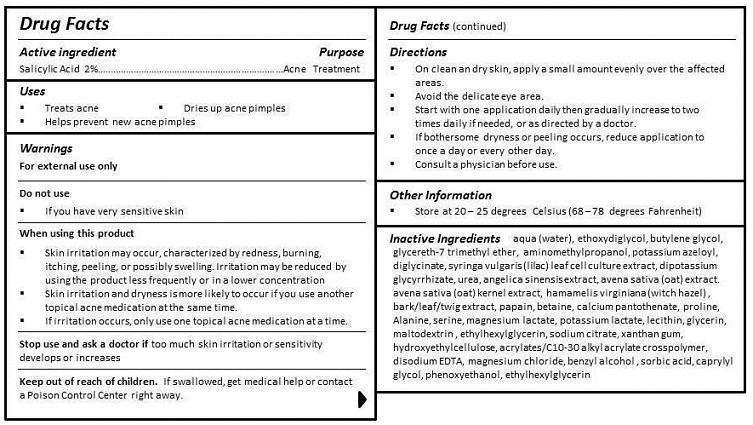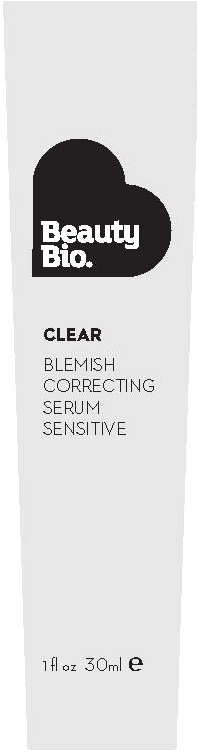 DRUG LABEL: BLEMISH CORRECTING SERUM
NDC: 54272-103 | Form: GEL
Manufacturer: CEN BEAUTY LLC
Category: otc | Type: HUMAN OTC DRUG LABEL
Date: 20130228

ACTIVE INGREDIENTS: SALICYLIC ACID 2 g/100 mL
INACTIVE INGREDIENTS: WATER; DIETHYLENE GLYCOL MONOETHYL ETHER; BUTYLENE GLYCOL; GLYCERETH-7 TRIMETHYL ETHER; AMINOMETHYLPROPANOL; POTASSIUM AZELOYL DIGLYCINATE; SYRINGA VULGARIS WHOLE; GLYCYRRHIZINATE DIPOTASSIUM; UREA; ANGELICA SINENSIS WHOLE; AVENA SATIVA TOP; HAMAMELIS VIRGINIANA ROOT BARK/STEM BARK; PAPAIN; BETAINE; CALCIUM PANTOTHENATE; PROLINE; ALANINE; SERINE; MAGNESIUM LACTATE; POTASSIUM LACTATE; LECITHIN, SOYBEAN; GLYCERIN; MALTODEXTRIN; ETHYLHEXYLGLYCERIN; SODIUM CITRATE; XANTHAN GUM; HYDROXYETHYL CELLULOSE (100 MPA.S AT 2%); CARBOMER COPOLYMER TYPE A (ALLYL PENTAERYTHRITOL CROSSLINKED); EDETATE DISODIUM; MAGNESIUM CHLORIDE; BENZYL ALCOHOL; SORBIC ACID; CAPRYLYL GLYCOL; PHENOXYETHANOL

ACTIVE INGREDIENT

SALICYLIC ACID 2%

PURPOSE

ACNE TREATMENT

USES

- TREATS ACNE
- DRIES UP ACNE PIMPLES
- HELPS PREVENT NEW ACNE PIMPLES

WARNINGS

FOR EXTERNAL USE ONLY

DO NOT USE

- IF YOU HAVE VERY SENSITIVE SKIN
- ARE SENSITIVE TO BENZOYL PEROXIDE

WHEN USING THIS PRODUCT

- SKIN IRRITATION MAY OCCUR, CHARACTERIZED BY REDNESS, BURNING, ITCHING, PEELING, OR POSSIBLY SWELLING. IRRITATION MAY BE REDUCED BY USING THE PRODUCT LESS FREQUENTLY OR IN A LOWER CONCENTRATION.
- SKIN IRRITATION AND DRYNESS IS MORE LIKELY TO OCCUR IF YOU USE ANOTHER TOPICAL ACNE MEDICATION AT THE SAME TIME.
- IF IRRITATION OCCURS, ONLY USE ONE TOPICAL ACNE MEDICATION AT A TIME.

STOP USE AND ASK A DOCTOR IF TOO MUCH SKIN IRRITATION OR SENSITIVITY DEVELOPS OR INCREASES.

KEEP OUT OF REACH OF CHILDREN. IF SWALLOWED, GET MEDICAL HELP OR CONTACT A POISON CONTROL CENTER RIGHT AWAY.

DIRECTIONS

- ON CLEAN AND DRY SKIN, APPLY A SMALL AMOUNT EVENLY OVER THE AFFECTED AREAS.
- AVOID THE DELICATE EYE AREA.
- START WITH ONE APPLICATION DAILY THEN GRADUALLY INCREASE TO TWO TIMES DAILY IF NEEDED, OR AS DIRECTED BY A DOCTOR.
- IF BOTHERSOME DRYNESS OR PEELING OCCURS, REDUCE APPLICATION TO ONCE A DAY OR EVERY OTHER DAY.
- CONSULT A PHYSICIAN BEFORE USE.

Other Information

Store at 20-25 DEGREES CELCIUS (68-78 DEGREES FAHRENHEIT)

INACTIVE INGREDIENT

INGREDIENTS

aqua (water), ethoxydiglycol, butylene glycol, glycereth-7 trimethyl ether, aminomethylpropanol, potassium azeloyl, diglycinate, syringa vulgaris (lilac) leaf cell culture extract, dipotassium glycyrrhizate, urea, angelica sinensis extract, avena sativa (oat) extract, avena sativa (oat) kernel extract, hamamelis virginiana (witch hazel) , bark/leaf/twig extract, papain, betaine, calcium pantothenate, proline, Alanine, serine, magnesium lactate, potassium lactate, lecithin, glycerin, maltodextrin , ethylhexylglycerin, sodium citrate, xanthan gum, hydroxyethylcellulose, acrylates/C10-30 alkyl acrylate crosspolymer, disodium EDTA, magnesium chloride, benzyl alcohol , sorbic acid, caprylyl glycol, phenoxyethanol, ethylhexylglycerin